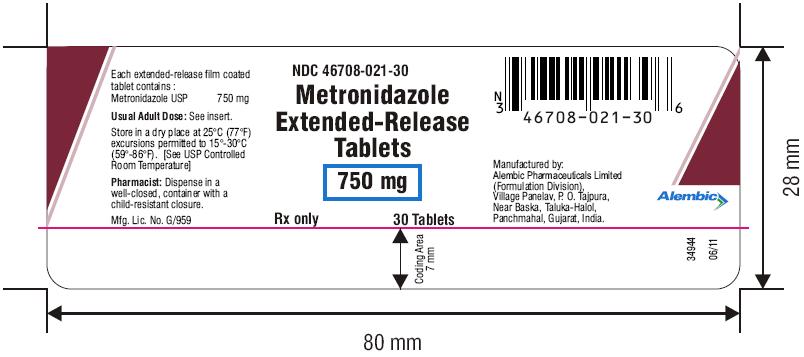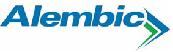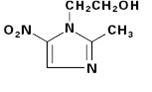 DRUG LABEL: Metronidazole
NDC: 46708-021 | Form: TABLET, FILM COATED, EXTENDED RELEASE
Manufacturer: Alembic Pharmaceuticals Limited
Category: prescription | Type: Human Prescription Drug Label
Date: 20230130

ACTIVE INGREDIENTS: METRONIDAZOLE 750 mg/1 1
INACTIVE INGREDIENTS: LACTOSE MONOHYDRATE; POVIDONE, UNSPECIFIED; MAGNESIUM STEARATE; POLYSORBATE 80; HYPROMELLOSE, UNSPECIFIED; TITANIUM DIOXIDE; POLYDEXTROSE; TRIACETIN; POLYETHYLENE GLYCOL 8000; FERRIC OXIDE YELLOW

Metronidazole Extended-Release Tablets
To reduce the development of drug-resistant bacteria and maintain the effectiveness of metronidazole extended-release tablets, and other antibacterial drugs, metronidazole extended-release tablets should be used only to treat or prevent infections that are proven or strongly suspected to be caused by bacteria.

WARNING

Metronidazole has been shown to be carcinogenic in mice and rats (see PRECAUTIONS). Unnecessary use of the drug should be avoided. Its use should be reserved for conditions described in the INDICATIONS AND USAGE section below.

DESCRIPTION

Metronidazole extended-release tablet is an oral formulation of the synthetic nitroimidazole antimicrobial agent, 2-methyl-5-nitro-1H-imidazole-1-ethanol, which has the following structural formula:

Metronidazole extended-release tablets, 750 mg contain 750 mg of metronidazole, USP. Inactive ingredients include lactose monohydrate, polyacrylate dispersion 30 percent, povidone, magnesium stearate, polysorbate 80, hypromellose, titanium dioxide, polydextrose, triacetin, polyethylene glycol and iron oxide yellow.

CLINICAL PHARMACOLOGY

Absorption

Disposition of metronidazole in the body is similar for both oral and intravenous dosage forms.

Metronidazole extended-release tablets, 750 mg tablets contain 750 mg of metronidazole in an extended release formulation which allows for once-daily dosing. The steady state pharmacokinetics were determined in 24 healthy adult female subjects with a mean ± SD age of 28.8 ± 8.8 years (range: 19 to 46).^2 The pharmacokinetic parameters of metronidazole after administration of metronidazole extended-release tablets, 750 mg under fed and fasting conditions are summarized in the following table.

Steady State Pharmacokinetic Parameters of Metronidazole after 750 mg of Metronidazole Extended-Release Tablets Given Once a Day for 7 Days

Parameter | Metronidazole Extended-Release Tablets, 750 mg daily Mean ± SD (N=24)
Parameter | fed | fasted
AUC(0–24) (μg•hr/mL) | 211 ± 60 | 198 ± 75.3
Cmax (μg/mL) | 19.4 ± 4.7 | 12.5 ± 4.8
Cmin (μg/mL) | 3.4 ± 2 | 4.2 ± 2.2
Tmax (hrs) | 4.6 ± 2.4 | 6.8 ± 2.8
T½ (hrs) | 7.4 ± 1.6 | 8.7 ± 2.2

Relative to the fasting state, the rate of metronidazole absorption from the extended release tablet is increased in the fed state resulting in alteration of the extended release characteristics.

Distribution

Metronidazole is the major component appearing in the plasma, with lesser quantities of metabolites also being present. Less than 20% of the circulating metronidazole is bound to plasma proteins. Metronidazole appears in cerebrospinal fluid, saliva, and breast milk in concentrations similar to those found in plasma. Bactericidal concentrations of metronidazole have also been detected in pus from hepatic abscesses.

Metabolism/Excretion

The major route of elimination of metronidazole and its metabolites is via the urine (60% to 80% of the dose), with fecal excretion accounting for 6% to 15% of the dose. The metabolites that appear in the urine result primarily from side-chain oxidation [1-(ß-hydroxyethyl)-2-hydroxymethyl-5-nitroimidazole and 2-methyl-5-nitroimidazole-1-yl-acetic acid] and glucuronide conjugation, with unchanged metronidazole accounting for approximately 20% of the total. Both the parent compound and the hydroxyl metabolite possess in vitro antimicrobial activity.

Renal clearance of metronidazole is approximately 10 mL/min/1.73 m^2. ^1The average elimination half-life of metronidazole in healthy subjects is eight hours.

Renal Impairment

Decreased renal function does not alter the single-dose pharmacokinetics of metronidazole.

Subjects with end-stage renal disease (ESRD; CLCR=8.1±9.1 mL/min) and who received a single intravenous infusion of metronidazole 500 mg had no significant change in metronidazole pharmacokinetics but had 2-fold higher Cmax of hydroxy-metronidazole and 5-fold higher Cmax of metronidazole acetate, compared to healthy subjects with normal renal function (CLCR=126±16 mL/min). Thus, on account of the potential accumulation of metronidazole metabolites in ESRD patients, monitoring for metronidazole associated adverse events is recommended (see PRECAUTIONS).

Effect of Dialysis

Following a single intravenous infusion or oral dose of metronidazole 500 mg, the clearance of metronidazole was investigated in ESRD subjects undergoing hemodialysis or continuous ambulatory peritoneal dialysis (CAPD). A hemodialysis session lasting for 4 to 8 hours removed 40% to 65% of the administered metronidazole dose, depending on the type of dialyzer membrane used and the duration of the dialysis session. If the administration of metronidazole cannot be separated from the dialysis session, supplementation of metronidazole dose following hemodialysis should be considered (see DOSAGE AND ADMINISTRATION). A peritoneal dialysis session lasting for 7.5 hours removed approximately 10% of the administered metronidazole dose. No adjustment in metronidazole dose is needed in ESRD patients undergoing CAPD.

Hepatic Impairment

Following a single intravenous infusion of 500 mg metronidazole, the mean AUC24 of metronidazole was higher by 114% in patients with severe (Child-Pugh C) hepatic impairment, and by 54% and 53% in patients with mild (Child-Pugh A), and moderate (Child-Pugh B) hepatic impairment, respectively, compared to healthy control subjects. There were no significant changes in the AUC24 of hydroxyl-metronidazole in these hepatically impaired patients. Metronidazole extended-release tablets should not be administered to patients with severe (Child-Pugh C) hepatic impairment unless it is deemed that the benefits outweigh the risks in these patients. No dosage adjustment is needed for patients with mild to moderate hepatic impairment. Patients with hepatic impairment who receive the usual recommended dose of metronidazole extended-release tablet should be monitored for metronidazole associated adverse events (see PRECAUTIONS and DOSAGE AND ADMINISTRATION).

Geriatric Patients

Following a single 500 mg oral or IV dose of metronidazole, subjects >70 years old with no apparent renal or hepatic dysfunction had a 40% to 80% higher mean AUC of hydroxy-metronidazole (active metabolite), with no apparent increase in the mean AUC of metronidazole (parent compound), compared to young healthy controls <40 years old. In geriatric patients, monitoring for metronidazole associated adverse events is recommended (see PRECAUTIONS).

Pediatric Patients

In one study, newborn infants appeared to demonstrate diminished capacity to eliminate metronidazole. The elimination half-life, measured during the first 3 days of life, was inversely related to gestational age. In infants whose gestational ages were between 28 and 40 weeks, the corresponding elimination half-lives ranged from 109 to 22.5 hours.

Microbiology

Mechanism of Action

Metronidazole, a nitroimidazole, exerts antibacterial effects in an anaerobic environment against most obligate anaerobes. Once metronidazole enters the organism by passive diffusion and activated in the cytoplasm of susceptible anaerobic bacteria, it is reduced; this process includes intra-cellular electron transport proteins such as ferredoxin, transfer of an electron to the nitro group of the metronidazole, and formation of a short-lived nitroso free radical. Because of this alteration of the metronidazole molecule, a concentration gradient is created and maintained which promotes the drug’s intracellular transport. The reduced form of metronidazole and free radicals can interact with DNA leading to inhibition of DNA synthesis and DNA degradation leading to death of bacteria. The precise mechanism of action of metronidazole is unclear.

Resistance

A potential for development of resistance exists against metronidazole.

Resistance may be due to multiple mechanisms that include decreased uptake of the drug, altered reduction efficiency, overexpression of the efflux pumps, inactivation of the drug, and/or increased DNA damage repair.

Metronidazole does not possess any clinically relevant activity against facultative anaerobes or obligate aerobes.

Antimicrobial activity

Bacteroides species

Gardnerella vaginalis

Mobiluncus species

Peptostreptococcus species

Susceptibility Testing

For specific information regarding susceptibility test interpretive criteria and associated test methods and quality control standards recognized by FDA for this drug, please see: https://www.fda.gov/STIC.

INDICATIONS AND USAGE

Bacterial Vaginosis (BV). Metronidazole extended-release 750 mg tablets are indicated in the treatment of BV in non-pregnant women.

To reduce the development of drug-resistant bacteria and maintain the effectiveness of metronidazole extended-release tablets and other antibacterial drugs, metronidazole extended-release tablets should be used only to treat or prevent infections that are proven or strongly suspected to be caused by susceptible bacteria. When culture and susceptibility information are available, they should be considered in selecting or modifying antibacterial therapy. In the absence of such data, local epidemiology and susceptibility patterns may contribute to the empiric selection of therapy.

CONTRAINDICATIONS

Hypersensitivity

Metronidazole extended-release 750 mg tablets are contraindicated in patients with a prior history of hypersensitivity to metronidazole or other nitroimidazole derivatives.

Psychotic Reaction with Disulfiram

Use of oral metronidazole is associated with psychotic reactions in alcoholic patients who were using disulfiram concurrently. Do not administer metronidazole to patients who have taken disulfiram within the last two weeks (see PRECAUTIONS, Drug Interactions).

Interaction with Alcohol

Use of oral metronidazole is associated with a disulfiram-like reaction to alcohol, including abdominal cramps, nausea, vomiting, headaches, and flushing. Discontinue consumption of alcohol or products containing propylene glycol during and for at least three days after therapy with metronidazole (see PRECAUTIONS, Drug Interactions).

Cockayne Syndrome
Metronidazole Extended-Release 750 mg tablets are contraindicated in patients with Cockayne syndrome. Severe irreversible hepatotoxicity/acute liver failure with fatal outcomes have been reported after initiation of metronidazole in patients with Cockayne syndrome (see ADVERSE REACTIONS).

WARNINGS

Central and Peripheral Nervous System Effects

Encephalopathy and peripheral neuropathy: Cases of encephalopathy and peripheral neuropathy (including optic neuropathy) have been reported with metronidazole.

Encephalopathy has been reported in association with cerebellar toxicity characterized by ataxia, dizziness, and dysarthria. CNS lesions seen on MRI have been described in reports of encephalopathy. CNS symptoms are generally reversible within days to weeks upon discontinuation of metronidazole. CNS lesions seen on MRI have also been described as reversible.

Peripheral neuropathy, mainly of sensory type has been reported and is characterized by numbness or paresthesia of an extremity.

Convulsive seizures have been reported in patients treated with metronidazole.

Aseptic meningitis: Cases of aseptic meningitis have been reported with metronidazole. Symptoms can occur within hours of dose administration and generally resolve after metronidazole therapy is discontinued.

The appearance of abnormal neurologic signs and symptoms demands the prompt evaluation of the benefit/risk ratio of the continuation of therapy (see ADVERSE REACTIONS).

PRECAUTIONS

General

Hepatic Impairment

Patients with hepatic impairment metabolize metronidazole slowly, with resultant accumulation of metronidazole in the plasma. Metronidazole extended-release tablets should not be administered to patients with severe (Child-Pugh C) hepatic impairment unless it is deemed that the benefits outweigh the risks in these patients. For patients with mild to moderate hepatic impairment, no dosage adjustment is needed. Patients with hepatic impairment who receive the usual recommended dose of metronidazole extended-release tablets should be monitored for metronidazole associated adverse events (see CLINICAL PHARMACOLOGY and DOSAGE AND ADMINISTRATION).

Renal Impairment

Patients with end-stage renal disease may excrete metronidazole and metabolites slowly in the urine, resulting in significant accumulation of metronidazole metabolites. Monitoring for metronidazole associated adverse events is recommended (see CLINICAL PHARMACOLOGY).

Fungal Superinfections

Known or previously unrecognized candidiasis may present more prominent symptoms during therapy with metronidazole and requires treatment with a candidacidal agent.

Use in Patients with Blood Dyscrasias

Metronidazole is a nitroimidazole and should be used with caution in patients with evidence of or history of blood dyscrasia. A mild leucopenia has been observed during its administration; however, no persistent hematologic abnormalities attributable to metronidazole have been observed in clinical studies. Total and differential leukocyte counts are recommended before and after therapy.

Drug-Resistant Bacteria and Parasites

Prescribing metronidazole extended-release tablets in the absence of a proven or strongly suspected bacterial infection or a prophylactic indication is unlikely to provide benefit to the patient and increases the risk of the development of drug-resistant bacteria and parasites.

Information for patients

Interaction with Alcohol

Discontinue consumption of alcoholic beverages or products containing propylene glycol while taking metronidazole and for at least three days afterward because abdominal cramps, nausea, vomiting, headaches, and flushing may occur (see CONTRAINDICATIONS and PRECAUTIONS, Drug Interactions).

Treatment of Bacterial Infections

Patients should be counseled that metronidazole extended-release tablets should only be used to treat bacterial infections. Metronidazole extended-release tablet does not treat viral infections (e.g., the common cold). When metronidazole extended-release tablet is prescribed to treat a bacterial infection, patients should be told that although it is common to feel better early in the course of therapy, the medication should be taken exactly as directed. Skipping doses or not completing the full course of therapy may (1) decrease the effectiveness of the immediate treatment and (2) increase the likelihood that bacteria will develop resistance and will not be treatable by metronidazole extended-release tablets in the future.

Drug interactions

Disulfiram

Psychotic reactions have been reported in alcoholic patients who are using metronidazole and disulfiram concurrently. Metronidazole should not be given to patients who have taken disulfiram within the last 2 weeks (see CONTRAINDICATIONS).

Alcoholic Beverages

Abdominal cramps, nausea, vomiting, headaches, and flushing may occur if alcoholic beverages or products containing propylene glycol are consumed during or following metronidazole therapy (see CONTRAINDICATIONS).

Warfarin and other Oral Anticoagulants

Metronidazole has been reported to potentiate the anticoagulant effect of warfarin and other oral coumarin anticoagulants, resulting in a prolongation of prothrombin time. When metronidazole 375 capsules is prescribed for patients on this type of anticoagulant therapy, prothrombin time and INR should be carefully monitored.

Lithium

In patients stabilized on relatively high doses of lithium, short-term metronidazole therapy has been associated with elevation of serum lithium and, in a few cases, signs of lithium toxicity. Serum lithium and serum creatinine levels should be obtained several days after beginning metronidazole to detect any increase that may precede clinical symptoms of lithium intoxication.

Busulfan

Metronidazole has been reported to increase plasma concentrations of busulfan, which can result in an increased risk for serious busulfan toxicity. Metronidazole should not be administered concomitantly with busulfan unless the benefit outweighs the risk. If no therapeutic alternatives to metronidazole are available, and concomitant administration with busulfan is medically needed, frequent monitoring of busulfan plasma concentration should be performed and the busulfan dose should be adjusted accordingly.

Drugs that Inhibit CYP450 Enzymes

The simultaneous administration of drugs that decrease microsomal liver enzyme activity, such as cimetidine, may prolong the half-life and decrease plasma clearance of metronidazole.

Drugs that Induce CYP450 Enzymes

The simultaneous administration of drugs that induce microsomal liver enzymes, such as phenytoin or phenobarbital, may accelerate the elimination of metronidazole, resulting in reduced plasma levels; impaired clearance of phenytoin has been reported.

Drugs that Prolong the QT interval

QT prolongation has been reported, particularly when metronidazole was administered with drugs with the potential for prolonging the QT interval.

Drug/Laboratory test interactions

Metronidazole may interfere with certain types of determinations of serum chemistry values, such as aspartate aminotransferase (AST, SGOT), alanine aminotransferase (ALT, SGPT), lactate dehydrogenase (LDH), triglycerides, and glucose hexokinase. Values of zero may be observed. All of the assays in which interference has been reported involve enzymatic coupling of the assay to oxidation-reduction of nicotinamide adenine dinucleotide (NAD^+⇄NADH). Interference is due to the similarity in absorbance peaks of NADH (340 nm) and metronidazole (322 nm) at pH 7.

Carcinogenesis, mutagenesis, impairment of fertility

Tumors affecting the liver, lung, mammary, and lymphatic tissues have been detected in several studies of metronidazole in rats and mice, but not hamsters.

Pulmonary tumors have been observed in all six reported studies in the mouse, including one study in which the animals were dosed on an intermittent schedule (administration during every fourth week only). Malignant liver tumors were increased in male mice treated at approximately 1500 mg/m^2 (about 3 times the recommended daily dose, based on body surface area comparisons). Malignant lymphomas and pulmonary neoplasms are also increased with lifetime feeding of the drug to mice. Mammary and hepatic tumors were increased among female rats administered oral metronidazole compared to concurrent controls. Two lifetime tumorigenicity studies in hamsters have been performed and reported to be negative.

Metronidazole has shown mutagenic activity in in vitro assay systems including the Ames test. Studies in mammals in vivo have failed to demonstrate a potential for genetic damage.

Metronidazole failed to produce any adverse effects on fertility or testicular function in male rats at doses up to 400 mg/kg/day (approximately 5 times the recommended dose based on body surface area comparisons) for 28 days. However, rats treated at the same dose for 6 weeks, or longer were infertile and showed severe degeneration of the seminiferous epithelium in the testes as well as marked decreases in testicular spermatid counts and epididymal sperm counts. Fertility was restored in most rats after an eight week, drug-free recovery period.

Pregnancy

Teratogenic effects:

There are no adequate and well-controlled studies of metronidazole extended-release tablets in pregnant women. There are published data from case-control studies, cohort studies, and 2-meta-analyses that include more than 5000 pregnant women who used metronidazole during pregnancy. Many studies included first trimester exposures. One study showed an increased risk of cleft lip, with or without cleft palate, in infants exposed to metronidazole in-utero; however, these finding were not confirmed. In addition, more than ten randomized placebo-controlled clinical trials enrolled more than 5000 pregnant women to assess the use of antibiotic treatment (including metronidazole) for bacterial vaginosis on the incidence of preterm delivery. Most studies did not show an increased risk for congenital anomalies or other adverse fetal outcomes following metronidazole exposure during pregnancy. Three studies conducted to assess the risk of infant cancer following metronidazole exposure during pregnancy did not show an increased risk; however, the ability of these studies to detect such a signal was limited.

Metronidazole crosses the placental barrier and its effects on the human fetal organogenesis are not known. Reproduction studies have been performed in rats, rabbits, and mice at doses about four times the recommended human dose based on body surface area comparisons. There was no evidence of harm to the fetus due to metronidazole.

Nursing mothers

Metronidazole is present in human milk at concentrations similar to maternal serum levels, and infant serum levels can be close to or comparable to infant therapeutic levels. Because of the potential for tumorigenicity shown for metronidazole in mouse and rat studies, a decision should be made whether to discontinue nursing or to discontinue the drug, taking into account the importance of the drug to the mother. Alternatively, a nursing mother may choose to pump and discard human milk for the duration of metronidazole therapy, and for 24 hours after therapy ends and feed her infant stored human milk or formula.

Geriatric use

In geriatric patients, monitoring for metronidazole associated adverse events is recommended (see CLINICAL PHARMACOLOGY, PRECAUTIONS). Decreased liver function in geriatric patients can result in increased concentrations of metronidazole that may necessitate adjustment of metronidazole dosage (see DOSAGE AND ADMINISTRATION).

Pediatric use

The safety and efficacy of metronidazole extended-release 750 mg tablets in the treatment of bacterial vaginosis in post-menarchal females has been established on the extrapolation of clinical trial data from adult women. The safety and efficacy of metronidazole extended- release 750 mg tablets in pre-menarchal females have not been established.

ADVERSE REACTIONS

In two multicenter clinical trials, a total of 270 patients received 750 mg metronidazole extended-release tablets orally once daily for 7 days, and 287 were treated with a comparator agent administered intravaginally once daily for 7 days (See CLINICAL STUDIES).^3,4

Most adverse events were described as being of mild or moderate severity. Among patients taking metronidazole extended-release tablets who reported headaches, 10% considered them severe, and less than 2% of reported episodes of nausea were considered severe. Metallic taste was reported by 9% of patients taking metronidazole extended-release tablets.

Adverse events reported at ≥2% incidence for either treatment group, irrespective of treatment causality, are summarized in the table below.

Adverse Events

(≥2% Incidence Rate)—Irrespective of Treatment Causality

 | Metronidazole Extended-Release Tablets 7 days (N=267) | Vaginal Preparation (N=285)
Headache | 48 (18%) | 44 (15%)
Vaginitis | 39 (15%) | 32 (12%)
Nausea | 28 (10%) | 8 (3%)
Taste Perversion (metallic taste) | 23 (9%) | 1 (0%)
Infection Bacterial | 19 (7%) | 17 (6%)
Influenza-like Symptoms | 17 (6%) | 20 (7%)
Pruritus Genital | 14 (5%) | 25 (9%)
Abdominal Pain | 10 (4%) | 13 (5%)
Dizziness | 11 (4%) | 3 (1%)
Diarrhea | 11 (4%) | 3 (1%)
Upper Respiratory Tract Infection | 11 (4%) | 10 (4%)
Rhinitis | 12 (4%) | 10 (4%)
Sinusitis | 7 (3%) | 6 (2%)
Urine Abnormal | 7 (3%) | 4 (1%)
Pharyngitis | 8 (3%) | 4 (1%)
Dysmenorrhea | 9 (3%) | 7 (2%)
Moniliasis | 9 (3%) | 8 (3%)
Mouth Dry | 5 (2%) | 2 (1%)
Urinary Tract Infection | 6 (2%) | 16 (6%)

Vulvovaginal candidiasis is a recognized consequence of treatment with many anti-infective agents. In these multicenter clinical trials, there were no statistically significant differences in the incidence rates of yeast vaginitis for groups of patients treated with metronidazole extended-release tablets or the vaginal comparator.

The following reactions have been reported during treatment with metronidazole:

Central Nervous System: The most serious adverse reactions reported in patients treated with metronidazole have been convulsive seizures, encephalopathy, aseptic meningitis, optic and peripheral neuropathy, the latter characterized mainly by numbness or paresthesia of an extremity. Since persistent peripheral neuropathy has been reported in some patients receiving prolonged administration of metronidazole, patients should be specifically warned about these reactions and should be told to stop the drug and report immediately to their physicians if any neurologic symptoms occur. In addition, patients have reported headache, syncope, dizziness, vertigo, incoordination, ataxia, confusion, dysarthria, irritability, depression, weakness, and insomnia (See WARNINGS).

Gastrointestinal: The most common adverse reactions reported have been referable to the gastrointestinal tract, particularly nausea, sometimes accompanied by headache, anorexia, and occasionally vomiting, diarrhea, epigastric distress; abdominal cramping; and constipation.

Mouth: A sharp, unpleasant metallic taste is not unusual. Furry tongue, glossitis, and stomatitis have occurred; these may be associated with a sudden overgrowth of Candida which may occur during therapy.

Dermatologic: Erythematous rash and pruritus.

Hematopoietic: Reversible neutropenia (leukopenia); rarely, reversible thrombocytopenia.

Cardiovascular: QT prolongation has been reported, particularly when metronidazole was administered with drugs with the potential for prolonging the QT interval. Flattening of the T-wave may be seen in electrocardiographic tracings.

Hypersensitivity: Urticaria, erythematous rash, Stevens-Johnson Syndrome, toxic epidermal necrolysis, flushing, nasal congestion, dryness of the mouth (or vagina or vulva), and fever.

Renal: Dysuria, cystitis, polyuria, incontinence, and a sense of pelvic pressure. Instances of darkened urine have been reported by approximately one patient in 100,000. Although the pigment which is probably responsible for this phenomenon has not been positively identified, it is almost certainly a metabolite of metronidazole and seems to have no clinical significance.

Hepatic: Cases of severe irreversible hepatotoxicity/acute liver failure, including cases with fatal outcomes with very rapid onset after initiation of systemic use of metronidazole, have been reported in patients with Cockayne Syndrome (latency from drug start to signs of liver failure as short as 2 days) (see CONTRAINDICATIONS).

Other: Proliferation of Candida in the vagina, dyspareunia, decrease of libido, proctitis, and fleeting joint pains sometimes resembling “serum sickness.” Rare cases of pancreatitis, which generally abated on withdrawal of the drug, have been reported. Patients with Crohn’s disease are known to have an increased incidence of gastrointestinal and certain extraintestinal cancers. There have been some reports in the medical literature of breast and colon cancer in Crohn’s disease patients who have been treated with metronidazole at high doses for extended periods of time. A cause and effect relationship has not been established. Crohn’s disease is not an approved indication for metronidazole extended-release 750 mg tablets.

OVERDOSAGE

Single oral doses of metronidazole, up to 15 g, have been reported in suicide attempts and accidental overdoses. Symptoms reported include nausea, vomiting, and ataxia.

Oral metronidazole has been studied as a radiation sensitizer in the treatment of malignant tumors. Neurotoxic effects, including seizures and peripheral neuropathy, have been reported after 5 to 7 days of doses of 6 g to 10.4 g every other day.

Treatment of Overdosage: There is no specific antidote for metronidazole overdose; therefore, management of the patient should consist of symptomatic and supportive therapy.

DOSAGE AND ADMINISTRATION

Bacterial Vaginosis: 750 mg once daily by mouth for seven consecutive days.

Metronidazole extended-release 750 mg tablets should be taken under fasting conditions, at least one hour before or two hours after meals. The optimum extended-release characteristics of metronidazole extended-release tablets 750 mg are obtained when the drug is taken under fasting conditions (See CLINICAL PHARMACOLOGY, Absorption).

Metronidazole extended-release tablets should not be split, chewed, or crushed.

Dosage Adjustments

Patients Undergoing Hemodialysis

Hemodialysis removes significant amounts of metronidazole and its metabolites from systemic circulation. The clearance of metronidazole will depend on the type of dialysis membrane used, the duration of the dialysis session, and other factors. If the administration of metronidazole cannot be separated from a hemodialysis session, supplementation of metronidazole dosage following the hemodialysis session should be considered, depending on the patient’s clinical situation (see CLINICAL PHARMACOLOGY).

HOW SUPPLIED

Metronidazole extended-release tablets, 750 mg are Yellow, oblong, biconvex film coated tablets debossed with L106 on one side and plain on other side, and supplied as:

NDC Number Size

46708-021-30 Bottle of 30

46708-021-50 Bottle of 50

46708-021-31 Bottle of 100

46708-021-71 Bottle of 500

Storage and Stability: Store in a dry place at 25°C (77°F); excursions permitted to 15°-30°C (59°-86°F). [See USP Controlled Room Temperature.] Dispense in a well-closed container with a child-resistant closure.

CLINICAL STUDIES

Bacterial vaginosis (BV) is a clinical syndrome that results from a replacement of the normal, Lactobacillus-dominant flora with several other organisms including Gardnerella vaginalis, Mobiluncus spp, Mycoplasma hominis and anaerobes (Peptostreptococcus spp and Bacteroides spp).

Metronidazole extended-release tablet was studied in patients with BV in two randomized, multicenter, well-controlled, investigator blind clinical trials.^3,4 A total of 557 otherwise healthy nonpregnant patients with BV were randomized to treatment with metronidazole extended-release tablets once a day for 7 days (n=270) or 2% clindamycin vaginal cream one applicator full (5 grams) once a day for 7 days (n=287).

The primary efficacy endpoint for each treatment regimen was defined as clinical cure assessed at 28 to 32 days post-therapy. Clinical cure was defined as a return to normal of the vaginal pH (≤4.5), absence of a “fishy” amine odor, and absence of clue cells.

The study results are presented in the table below:

Clinical Cure Rates at One Month

 | Metronidazole extended-release tablets % (n/N) | 2% clindamycin cream % (n/N)
Study 1 | 61% (77/126) | 59% (80/135)
Study 2 | 62% (74/119)* | 43% (50/117)

*p<0.05 versus clindamycin cream

At one month post-therapy the pH of the vagina returned to normal earlier and in a greater percentage of patients in the metronidazole extended-release tablets treatment group when compared to the 2% clindamycin vaginal cream group; 72% vs. 65%, respectively. Likewise, metronidazole extended-release tablets restored the normal Lactobacillus-predominant vaginal flora in a larger percentage of patients at one month post-therapy when compared to the 2% clindamycin treated group; 74% vs. 63%, respectively.

REFERENCES

1. Salas-Herrera IG, Pearson RM, Johnston A, and Turner P. Concentration of metronidazole in cervical mucus and serum after single and repeated oral doses. J Antimicrobial Chemotherapy 1991; 28:283–289.
2. Metronidazole modified-release tablet multiple-dose bioequivalency study (fed/fasting). G.D. Searle & Co., Protocol No. S13-94-02-014; Report No. S13-95-060-14, 11 July 1995.
3. Integrated clinical and statistical report for the treatment of bacterial vaginosis with metronidazole modified release tablet- a dose duration study. G.D. Searle & Co., Protocol No. N13-95-02-015; Report No. N13-96-06-015, 19 Nov 1996.
4. Integrated clinical and statistical report for the treatment of bacterial vaginosis with metronidazole modified release tablet. G.D. Searle & Co., Protocol No. N13-95-02-017; Report No. N13-96-06-017, 11 Nov 1996. Call your doctor for medical advice about side effects. You may report side effects to FDA at 1-800-FDA-1088.

Call your doctor for medical advice about side effects. You may report side effects to FDA at 1-800-FDA-1088.
Rx only

Manufactured by:
Alembic Pharmaceuticals Limited
(Formulation Division),
Village Panelav, P. O. Tajpura, Near Baska,
Taluka-Halol, Panchmahal, Gujarat, India.
Revised: 09/2021

PACKAGE LABEL.PRINCIPAL DISPLAY PANEL

NDC 46708-021-30
Metronidazole
Extended-Release
Tablets
750 mg
Rx only
30 Tablets